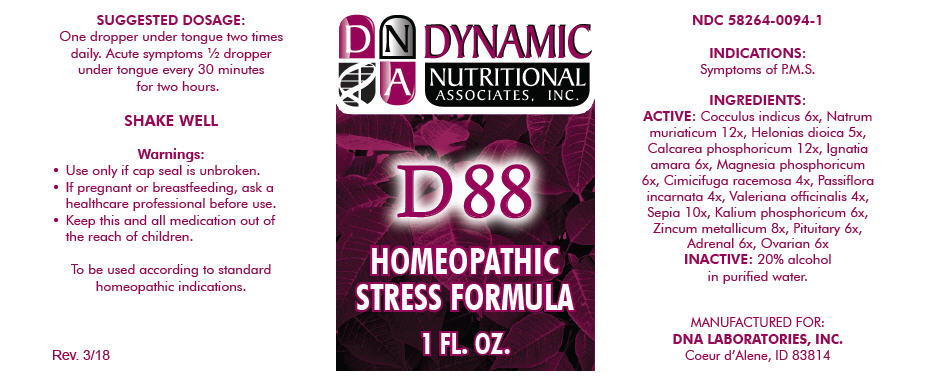 DRUG LABEL: D-88
NDC: 58264-0094 | Form: SOLUTION
Manufacturer: DNA Labs, Inc.
Category: homeopathic | Type: HUMAN OTC DRUG LABEL
Date: 20250113

ACTIVE INGREDIENTS: ANAMIRTA COCCULUS SEED 6 [hp_X]/1 mL; SODIUM CHLORIDE 12 [hp_X]/1 mL; CHAMAELIRIUM LUTEUM ROOT 5 [hp_X]/1 mL; TRIBASIC CALCIUM PHOSPHATE 12 [hp_X]/1 mL; STRYCHNOS IGNATII SEED 6 [hp_X]/1 mL; MAGNESIUM PHOSPHATE, DIBASIC TRIHYDRATE 6 [hp_X]/1 mL; BLACK COHOSH 4 [hp_X]/1 mL; PASSIFLORA INCARNATA FLOWERING TOP 4 [hp_X]/1 mL; VALERIAN 4 [hp_X]/1 mL; SEPIA OFFICINALIS JUICE 10 [hp_X]/1 mL; DIBASIC POTASSIUM PHOSPHATE 6 [hp_X]/1 mL; BOS TAURUS PITUITARY GLAND, POSTERIOR 6 [hp_X]/1 mL; ZINC 8 [hp_X]/1 mL; BOS TAURUS ADRENAL GLAND 6 [hp_X]/1 mL; BOS TAURUS OVARY 6 [hp_X]/1 mL
INACTIVE INGREDIENTS: ALCOHOL; WATER

D-88

NDC 58264-0094-1

INDICATIONS

PURPOSE

Symptoms of P.M.S.

INGREDIENTS

ACTIVE

Cocculus indicus 6x, Natrum muriaticum 12x, Helonias dioica 5x, Calcarea phosphoricum 12x, Ignatia amara 6x, Magnesia phosphoricum 6x, Cimicifuga racemosa 4x, Passiflora incarnata 4x, Valeriana officinalis 4x, Sepia 10x, Kalium phosphoricum 6x, Zincum metallicum 8x, Pituitary 6x, Adrenal 6x, Ovarian 6x

INACTIVE

20% alcohol in purified water.

SUGGESTED DOSAGE

One dropper under tongue two times daily. Acute symptoms ½ dropper under tongue every 30 minutes for two hours.

STORAGE AND HANDLING

SHAKE WELL

Warnings

- Use only if cap seal is unbroken.

PREGNANCY OR BREAST FEEDING

- If pregnant or breastfeeding, ask a healthcare professional before use.

KEEP OUT OF REACH OF CHILDREN

- Keep this and all medication out of the reach of children.

To be used according to standard homeopathic indications.

PRINCIPAL DISPLAY PANEL - 1 FL. OZ. Bottle Label

DYNAMIC
NUTRITIONAL
ASSOCIATES, INC.

D 88

HOMEOPATHIC
STRESS FORMULA

1 FL. OZ.